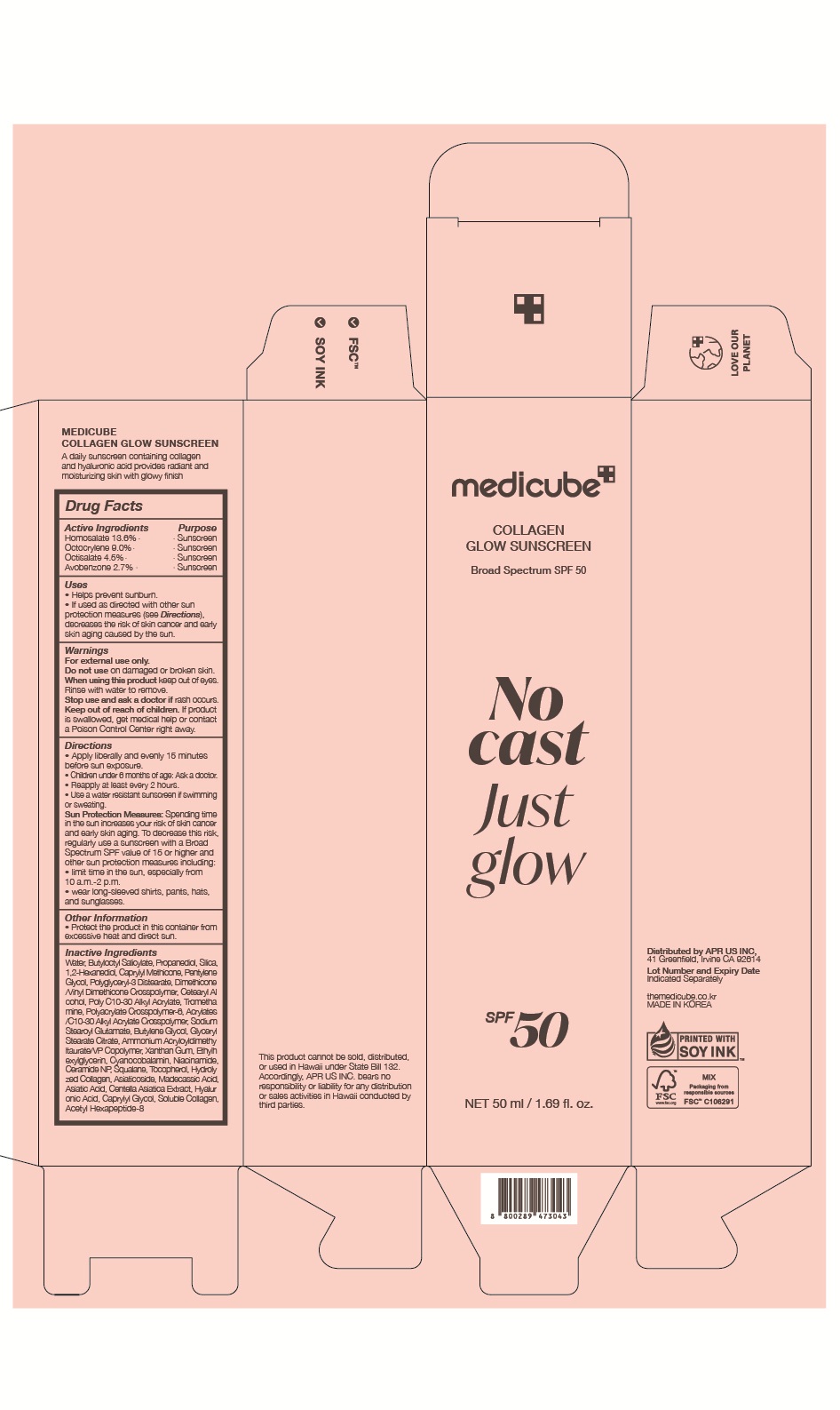 DRUG LABEL: MEDICUBE COLLAGEN GLOW SUNSCREEN
NDC: 82440-100 | Form: LOTION
Manufacturer: APR US INC
Category: otc | Type: HUMAN OTC DRUG LABEL
Date: 20250903

ACTIVE INGREDIENTS: OCTISALATE 4.5 g/100 mL; OCTOCRYLENE 9 g/100 mL; HOMOSALATE 13.6 g/100 mL; AVOBENZONE 2.7 g/100 mL
INACTIVE INGREDIENTS: WATER; BUTYLOCTYL SALICYLATE; CAPRYLYL METHICONE; 1,2-HEXANEDIOL; PROPANEDIOL

PMEKR61011R00
SMEUS66003R00

DOSAGE & ADMINISTRATION

Directions
• Apply liberally and evenly 15 minutes before sun exposure.
• Children under 6 months of age: Ask a doctor.
• Reapply at least every 2 hours.
• Use a water resistant sunscreen if swimming or sweating.
Sun Protection Measures: Spending time in the sun increases your risk of skin cancer and early skin aging. To decrease this risk, regularly use a sunscreen with a Broad Spectrum SPF value of 15 or higher and other sun protection measures including:
• limit time in the sun, especially from 10 a.m.-2 p.m.
• wear long-sleeved shirts, pants, hats, and sunglasses.

Inactive Ingredients

WATER, BUTYLOCTYL SALICYLATE, PROPANEDIOL, SILICA, 1,2-HEXANEDIOL, CAPRYLYL METHICONE, PENTYLENE GLYCOL, POLYGLYCERYL-3 DISTEARATE, DIMETHICONE/VINYL DIMETHICONE CROSSPOLYMER, CETEARYL ALCOHOL, POLY C10-30 ALKYL ACRYLATE, TROMETHAMINE, POLYACRYLATE CROSSPOLYMER-6, ACRYLATES/C10-30 ALKYL ACRYLATE CROSSPOLYMER, SODIUM STEAROYL GLUTAMATE, BUTYLENE GLYCOL, GLYCERYL STEARATE CITRATE, AMMONIUM ACRYLOYLDIMETHYLTAURATE/VP COPOLYMER, XANTHAN GUM, ETHYLHEXYLGLYCERIN, CYANOCOBALAMIN, NIACINAMIDE, CERAMIDE NP, SQUALANE, TOCOPHEROL, HYDROLYZED COLLAGEN, ASIATICOSIDE, MADECASSIC ACID, ASIATIC ACID, CENTELLA ASIATICA EXTRACT, HYALURONIC ACID, CAPRYLYL GLYCOL, SOLUBLE COLLAGEN, ACETYL HEXAPEPTIDE-8

Indications and Usage

Uses
• Helps prevent sunburn.
• If used as directed with other sun protection measures (see Directions), decreases the risk of skin cancer and early skin aging caused by the sun.

Warnings

- For external use only.
- Do not use on damaged or broken skin.
- When using this product keep out of eyes. Rinse with water to remove.
- Stop use and ask a doctor if rash occurs.
- Keep out of reach of children. If product is swallowed, get medical help or contact a Poison Control Center right away

Purpose

Sunscreen

Keep out of reach of children

If product is swallowed, get medical help or contact a Poison Control Center right away.